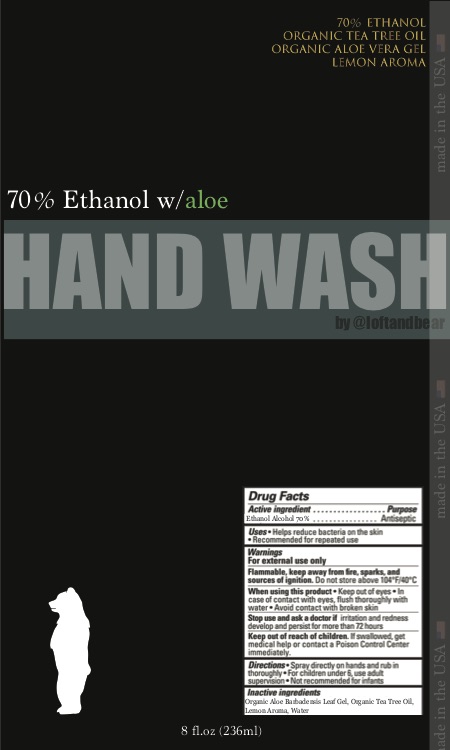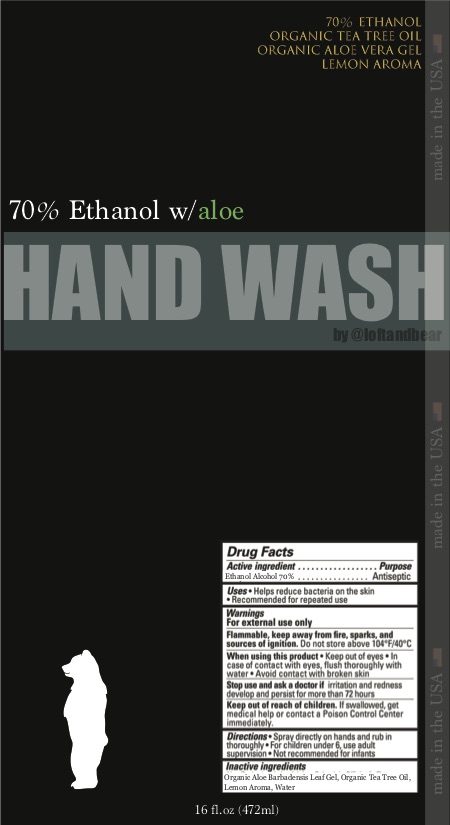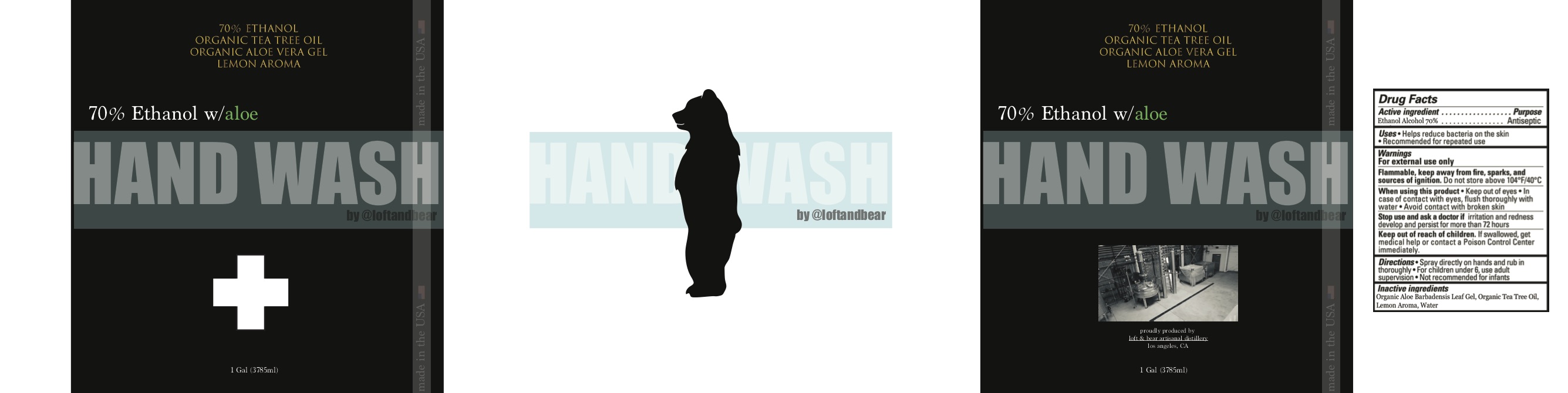 DRUG LABEL: Loft and Bear Hand Wash with Ethanol Alcohol 16 oz
NDC: 77179-7016 | Form: LIQUID
Manufacturer: Y. SA, INC
Category: otc | Type: HUMAN OTC DRUG LABEL
Date: 20200505

ACTIVE INGREDIENTS: ALCOHOL 473 mL/473 mL
INACTIVE INGREDIENTS: ALOE VERA LEAF 473 mL/473 mL; TEA TREE OIL 473 mL/473 mL; WATER 473 mL/473 mL

Loft and Bear Hand Wash with Ethanol Alcohol

The hand sanitizer is manufactured using only the following United States Pharmacopoeia (USP) grade ingredients in the preparation of the product (percentage in final product formulation)

1. Alcohol (ethanol) (USP or Food Chemical Codex (FCC) grade) (70%, volume/volume (v/v)) in an aqueous solution denatured according to Alcohol and Tobacco Tax and Trade Bureau regulations in 27 CFR part 20.
2. Sterile distilled water (26.5% v/v).
3. Aloe Barbadensis Leaf liquid (3.2% v/v).
4. Tea Tree Oil (0.3% v/v)

Active Ingredient(s)

Alcohol 70% v/v. Purpose: Antiseptic

Purpose

Antiseptic, Hand Sanitizer

Use

Hand Sanitizer to help reduce bacteria that potentially can cause disease. For use when soap and water are not available.

Warnings

For external use only. Flammable. Keep away from heat or flame

Do not use

- in children less than 2 months of age
- on open skin wounds

When using this product keep out of eyes, ears, and mouth. In case of contact with eyes, rinse eyes thoroughly with water.
Stop use and ask a doctor if irritation or rash occurs. These may be signs of a serious condition.
Keep out of reach of children. If swallowed, get medical help or contact a Poison Control Center right away.

Stop use and ask a doctor if irritation or rash occurs. These may be signs of a serious condition.

Keep out of reach of children. If swallowed, get medical help or contact a Poison Control Center right away.

Directions

- Place enough product on hands to cover all surfaces. Rub hands together until dry.
- Supervise children under 6 years of age when using this product to avoid swallowing.

Other information

- Store between 15-30C (59-86F)
- Avoid freezing and excessive heat above 40C (104F)

Inactive ingredients

Aloe Barbadensis Leaf liquid, Tea Tree Oil, purified water USP

Package Label - Principal Display Panel

236 mL NDC: 77179-7008-1

473 mL NDC: 77179-7016-2

3785 mL NDC: 77179-7128-4